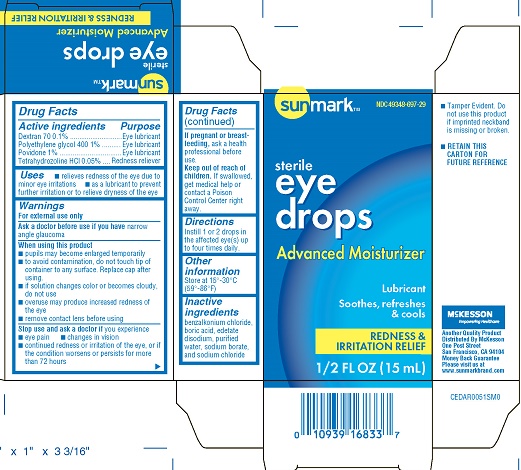 DRUG LABEL: Sunmark Eye Drops Advanced Moisturizer/Lubricant
NDC: 49348-697 | Form: SOLUTION/ DROPS
Manufacturer: Strategic Sourcing Services LLC
Category: otc | Type: HUMAN OTC DRUG LABEL
Date: 20231223

ACTIVE INGREDIENTS: DEXTRAN 70 0.1 g/100 mL; POLYETHYLENE GLYCOL 400 1 g/100 mL; POVIDONE 1 g/100 mL; TETRAHYDROZOLINE HYDROCHLORIDE 0.05 g/100 mL
INACTIVE INGREDIENTS: BENZALKONIUM CHLORIDE; EDETATE DISODIUM; WATER; SODIUM CHLORIDE; SODIUM BORATE; BORIC ACID

Sunmark Eye Drops Advanced Moisturizer/Lubricant (PLD)

Active Ingredients

Dextran 70 0.1%
povidone 1%
Polyethylene glycol 400 1%
Tetrahydrozoline HCL 0.05%

Purpose

Eye Lubricant

Redness reliever

Uses

- relieves redness of the eye due to minor eye irritations
- as a lubricant to prevent further irritation or to relieve dryness of the eye

Warnings

For external use only

Ask a doctor before use if you have

narrow angle glucoma

When using this product

- pupils may become enlarged temporarily
- to avoid contamination, do not touch tip of container to any surface. Replace cap after using.
- if solution changes color or become cloudy, do not use
- overuse may produce increased redness of the eye
- remove contact lens before using

Stop use and ask a doctor if you experience

- eye pain
- changes in vision
- continued redness or irritation of the eye, or if the condition worsens or persists for more than 72 hours

If pregnant or breast-feeding

ask a healthcare professional before use

Keep out of reach of children

If accidentally swallowed, get medical help or contact a Poison Control Center immediately

Directions

Instill 1 or 2 drops in the affected eye(s) up to four times daily.

Other information

Store at 15o- 30oC (59o- 86oF)

Inactive Ingredients

benzalkonium chloride, boric acid, edetate disodium, purified water, sodium borate, and sodium chloride